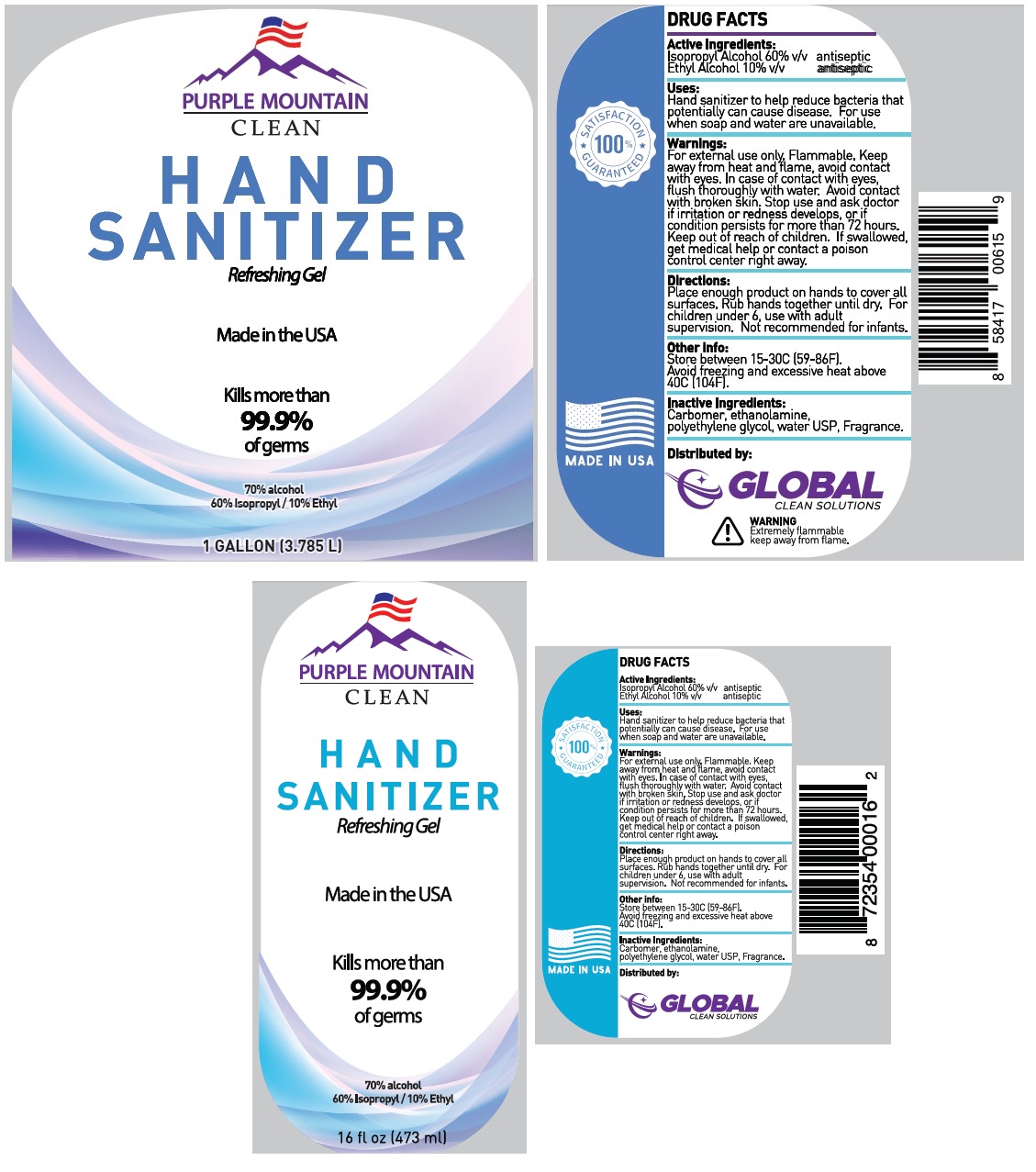 DRUG LABEL: Purple Mountain Clean Hand Sanitizer
NDC: 80120-101 | Form: GEL
Manufacturer: Edison Nation, Inc.
Category: otc | Type: HUMAN OTC DRUG LABEL
Date: 20200819

ACTIVE INGREDIENTS: ISOPROPYL ALCOHOL 60 L/100 L; ALCOHOL 10 L/100 L
INACTIVE INGREDIENTS: CARBOMER HOMOPOLYMER, UNSPECIFIED TYPE; MONOETHANOLAMINE; POLYETHYLENE GLYCOL, UNSPECIFIED; WATER

PURPLE MOUNTAIN CLEAN HAND SANITIZER

Active Ingredients:

Isopropyl Alcohol 60% v/v

Ethyl Alcohol 10% v/v

Purpose:

antiseptic

Uses:

Hand sanitizer to help reduce bacteria that potentially can cause disease. For use when soap and water are unavailable.

Warnings:

For external use only. Flammable. Keep away from heat and flame, avoid contact with eyes. In case of contact with eyes, flush thoroughly with water. Avoid contact with broken skin. Stop use and askdoctor if irritation or redness develops, or if condition persists for more than 72 hours

Keep out of reach of children. If swallowed, get medical help or contact a poison control center right away.

Directions :

Place enough product on hands to cover all surfaces. Rub hands together until dry. For children under 6, use with adult supervision. Not recommended for infants.

Other info:

Store between 15-30C (59-86F).

Avoid freezing and excessive heat above 40C (104F).

Inactive Ingredients:

Carbomer, ethanolamine, polyethylene glycol, water USP, Fragrance.

Refreshing Gel

Made in the USA

Kills more than 99.9% of germs

70%alcohol

60% Isopropyl /10% Ethyl

100% SATISFACTION

GUARANTEED

Distributed by:

GLOBAL CLEAN SOLUTIONS

WARNING

Extremely flammable